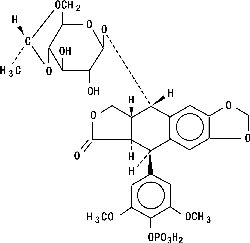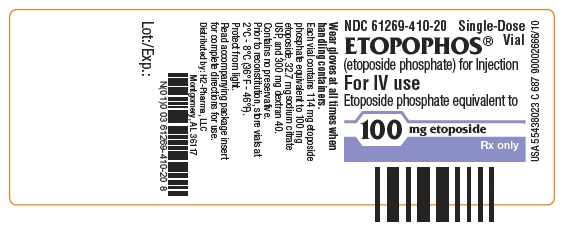 DRUG LABEL: ETOPOPHOS
NDC: 61269-410 | Form: INJECTION, POWDER, LYOPHILIZED, FOR SOLUTION
Manufacturer: H2-Pharma, LLC
Category: prescription | Type: HUMAN PRESCRIPTION DRUG LABEL
Date: 20251125

ACTIVE INGREDIENTS: etoposide phosphate 100 mg/1 1
INACTIVE INGREDIENTS: SODIUM CITRATE, UNSPECIFIED FORM 32.7 mg/1 1; DEXTRAN 40 300 mg/1 1

HIGHLIGHTS OF PRESCRIBING INFORMATION

These highlights do not include all the information needed to use ETOPOPHOS safely and effectively. See full prescribing information for ETOPOPHOS.
ETOPOPHOS® (etoposide phosphate) for injection,
for intravenous use
Initial U.S. Approval: 1983

1 INDICATIONS AND USAGE

ETOPOPHOS is a topoisomerase inhibitor indicated for the treatment of patients with:

- Refractory testicular tumors, in combination with other chemotherapeutic drugs. (1)
- Small cell lung cancer, in combination with cisplatin, as first-line treatment. (1)

2 DOSAGE AND ADMINISTRATION

- Refractory testicular tumors: 50 to 100 mg/m^2 per day administered intravenously over 5 minutes to 3.5 hours on days 1 through 5, or 100 mg/m^2 administered intravenously over 5 minutes to 3.5 hours on days 1, 3, and 5. (2.1)
- Small cell lung cancer: 35 mg/m^2 per day administered intravenously over 5 minutes to 3.5 hours for 4 days or 50 mg/m^2 per day administered intravenously over 5 minutes to 3.5 hours for 5 days. (2.2)
- Do not give by bolus injection. (2.4)
- Renal impairment: Reduce the recommended dose to 75% in patients with creatinine clearance 15 to 50 mL/min. (2.3)

3 DOSAGE FORMS AND STRENGTHS

For injection: 114 mg etoposide phosphate (equivalent to 100 mg etoposide), white to off-white, lyophilized powder in single-dose vial for reconstitution. (3, 11)

4 CONTRAINDICATIONS

Hypersensitivity to etoposide products. (4, 5.3)

5 WARNINGS AND PRECAUTIONS

- Myelosuppression: Obtain complete blood counts prior to each cycle and more frequently as clinically indicated. (5.1)
- Secondary leukemias: Can occur with long-term use. (5.2)
- Hypersensitivity reactions: Hypersensitivity reactions including anaphylaxis may occur. (5.3)
- Embryo-fetal toxicity: ETOPOPHOS can cause fetal harm. Advise females of potential risk to the fetus and to use effective contraception during treatment with ETOPOPHOS and for 6 months after final dose. Advise males to use effective contraception for 4 months, after the last dose of ETOPOPHOS. (5.4, 8.1, 8.3)

6 ADVERSE REACTIONS

Most common adverse reaction is neutropenia. (6)

To report SUSPECTED ADVERSE REACTIONS, contact the Safety Call Center at 1-866-885-0690 or FDA at 1-800-FDA-1088 or www.fda.gov/medwatch.

7 DRUG INTERACTIONS

Warfarin: Co-administration can result in elevated international normalized ratio (INR). Measure INR frequently. (7)

8 USE IN SPECIFIC POPULATIONS

Lactation: Do not breastfeed. (8.2)

FULL PRESCRIBING INFORMATION

1 INDICATIONS AND USAGE

1.1 Refractory Testicular Tumors

ETOPOPHOS is indicated, in combination with other chemotherapeutic drugs, for treatment of patients with refractory testicular tumors.

1.2 Small Cell Lung Cancer

ETOPOPHOS is indicated, in combination with cisplatin, for first-line treatment of patients with small cell lung cancer.

2 DOSAGE AND ADMINISTRATION

2.1 Refractory Testicular Tumors

The recommended dose of ETOPOPHOS is:

- 50 to 100 mg/m^2 per day administered intravenously over 5 minutes to 3.5 hours on days 1 through 5 of each 21-day (or 28-day cycle), or
- 100 mg/m^2 administered intravenously over 5 minutes to 3.5 hours on days 1, 3, and 5 of each 21-day (or 28-day cycle).

2.2 Small Cell Lung Cancer

The recommended dose of ETOPOPHOS is:

• 35 mg/m^2 per day administered intravenously over 5 minutes to 3.5 hours for 4 days, or
• 50 mg/m^2 per day administered intravenously over 5 minutes to 3.5 hours for 5 days.

2.3 Dosage Modification

In patients with a creatinine clearance (CLcr) 15-50 mL/min, administer 75% of the recommended dose.
Data are not available in patients with CLcr less than 15 mL/min. Consider further dose reduction in these patients.

2.4 Preparation and Administration

Preparation

- Reconstitute with Sterile Water for Injection, USP; 5% Dextrose Injection, USP; 0.9% Sodium Chloride Injection, USP; Bacteriostatic Water for Injection with Benzyl Alcohol; or Bacteriostatic Sodium Chloride for Injection with Benzyl Alcohol, using the quantity of diluent shown below:

Vial Strength | Volume of Diluent | Final Concentration
100 mg | 5 mL | 20 mg/mL
100 mg | 10 mL | 10 mg/mL

- Following reconstitution, ETOPOPHOS can be further diluted to concentrations as low as 0.1 mg/mL with either 5% Dextrose Injection, USP, or 0.9% Sodium Chloride Injection, USP.

- Inspect parenteral drug products visually for particulate matter and discoloration prior to administration whenever solution and container permit.

Storage
After reconstitution, store under the following conditions:

- Refrigerated 2° to 8°C (36° to 46°F) for 7 days;

- Room temperature at 20° to 25°C (68° to 77°F) for 24 hours following reconstitution with Sterile Water for Injection, USP, 5% Dextrose Injection, USP, or 0.9% Sodium Chloride Injection, USP;

- Room temperature 20° to 25°C (68° to 77°F) for 48 hours following reconstitution with Bacteriostatic Water for Injection with benzyl alcohol or Bacteriostatic Sodium Chloride for Injection with benzyl alcohol.

Reconstituted ETOPOPHOS solutions further diluted as directed can be stored under refrigeration 2° to 8°C (36° to 46°F) or at room temperature 20° to 25°C (68° to 77°F) for 24 hours.

Administration
DO NOT GIVE ETOPOPHOS BY BOLUS INTRAVENOUS INJECTION. ETOPOPHOS solutions may be administered at infusion rates up to 3.5 hours. Extravasation of ETOPOPHOS may result in swelling, pain, cellulitis, and necrosis including skin necrosis.

ETOPOPHOS is a cytotoxic drug. Follow applicable special handling and disposal procedures.^1 To minimize the risk of dermal exposure, use of gloves is recommended. If dermal contact occurs, immediately and thoroughly wash areas of skin contact with soap and water and flush mucosa with water.

3 DOSAGE FORMS AND STRENGTHS

For injection: 114 mg etoposide phosphate (equivalent to 100 mg etoposide), white to off-white, lyophilized powder in single-dose vial for reconstitution [see Description (11)].

4 CONTRAINDICATIONS

ETOPOPHOS is contraindicated in patients with a history of a severe hypersensitivity reaction to etoposide products [see Warnings and Precautions (5.3)].

5 WARNINGS AND PRECAUTIONS

5.1 Myelosuppression

ETOPOPHOS causes myelosuppression that results in thrombocytopenia and neutropenia. Fatal infections and bleeding have occurred. Obtain complete blood counts prior to each cycle of ETOPOPHOS and more frequently as clinically indicated [see Adverse Reactions (6.1)].

5.2 Secondary Leukemias

Secondary leukemias have occurred with long term use of ETOPOPHOS.

5.3 Hypersensitivity Reactions

ETOPOPHOS can cause hypersensitivity reactions, including rash, urticaria, pruritus, and anaphylaxis [see Adverse Reactions (6.1)]. If hypersensitivity reactions occur, immediately interrupt ETOPOPHOS and institute supportive management. Permanently discontinue ETOPOPHOS in patients who experience a severe hypersensitivity reaction.

5.4 Embryo-Fetal Toxicity

Based on animal studies and its mechanism of action, ETOPOPHOS can cause fetal harm when administered to a pregnant woman. Advise pregnant women of the potential hazard to the fetus [see Use in Specific Populations (8.1)].

Advise females of reproductive potential to use effective contraception during treatment with ETOPOPHOS and for at least 6 months after the final dose. Advise males with female partners of reproductive potential to use effective contraception for 4 months after the final dose [see Use in Specific Populations (8.3)].

6 ADVERSE REACTIONS

The following serious adverse reactions are described elsewhere in the labeling:

- Myelosuppression [see Warnings and Precautions (5.1)]
- Secondary leukemias [see Warnings and Precautions (5.2)]
- Hypersensitivity reactions [see Warnings and Precautions (5.3)]

6.1 Clinical Trials Experience

Because clinical trials are conducted under widely varying conditions, adverse reaction rates, observed in the clinical trials of a drug, cannot be directly compared to rates in the clinical trials of another drug and may not reflect the rates observed in practice.

ETOPOPHOS has been used as a single agent in clinical studies involving 206 patients with a variety of malignancies (including one non-Hodgkin’s lymphoma) and in combination with cisplatin in 60 patients with small cell lung cancer. The most common adverse reaction was neutropenia.

Other Important Adverse Reactions
Gastrointestinal Toxicity
Nausea and vomiting are the major gastrointestinal toxicities. The severity of nausea and vomiting is generally mild to moderate, with treatment discontinuation required in 1% of patients. Nausea and vomiting are managed with standard antiemetic therapy.

Other Toxicities
Other clinically important adverse reactions in clinical trials were:
Gastrointestinal: abdominal pain, constipation, dysphagia
General: fever
Ocular: transient cortical blindness, optic neuritis
Respiratory: interstitial pneumonitis/pulmonary fibrosis
Skin: pigmentation, radiation recall dermatitis, Stevens-Johnson syndrome, and toxic epidermal necrolysis
Neurologic: seizure, aftertaste
Hepatobiliary disorder: hepatotoxicity

6.2 Postmarketing Experience

The following adverse reactions have been identified during postapproval use of ETOPOPHOS. Because these reactions are reported voluntarily from a population of uncertain size, it is not always possible to reliably estimate their frequency or establish a causal relationship to drug exposure.

Extravasation
Extravasation, resulting in local soft tissue toxicity. Extravasation of ETOPOPHOS can result in swelling, pain, cellulitis, and necrosis, including skin necrosis.

Acute Renal Failure
Reversible cases of acute renal failure have been reported with administration of high dose (2220 mg/m^2) ETOPOPHOS with total body irradiation used for hematopoietic stem cell transplantation. The ETOPOPHOS formulation contains dextran 40, which has been associated with acute renal failure when administered in high doses.

7 DRUG INTERACTIONS

Warfarin: Co-administration of ETOPOPHOS with warfarin can result in elevated international normalized ratio (INR). Measure INR frequently.

8 USE IN SPECIFIC POPULATIONS

8.1 Pregnancy

Risk Summary
Based on animal data and its mechanism of action, ETOPOPHOS can cause fetal harm when administered to a pregnant woman. Etoposide, the active moiety of etoposide phosphate is teratogenic in mice and rats (see Data). Advise pregnant women of the potential hazard to a fetus.
Advise women of childbearing potential to avoid becoming pregnant.
In the U.S. general population, the estimated background risk of major birth defects and miscarriage in clinically recognized pregnancies is 2% to 4% and 15% to 20%, respectively.

Data
Animal Data
In rats, an intravenous etoposide dose of 0.4 mg/kg/day (about 0.05 times of the 50 mg/m^2 human dose based on body surface area [BSA]) during organogenesis caused maternal toxicity, embryotoxicity, and teratogenicity (skeletal abnormalities, exencephaly, encephalocele, and anophthalmia); higher doses of 1.2 and 3.6 mg/kg/day (about 0.14 and 0.5 times the 50 mg/m^2 human dose based on BSA) resulted in 90% and 100% embryonic resorptions. In mice, a single etoposide dose of 1.0 mg/kg (approximately 0.06 times the 50 mg/m^2 human dose based on BSA) administered intraperitoneally on days 6, 7, or 8 of gestation caused embryotoxicity, cranial abnormalities, and major skeletal malformations. An intraperitoneal dose of 1.5 mg/kg (about 0.1 times the 50 mg/m^2 human based on BSA) on day 7 of gestation caused an increase in the incidence of intrauterine death and fetal malformations and a significant decrease in the average fetal body weight [see Nonclinical Toxicology (13.1)].

8.2 Lactation

There is no information regarding the presence of etoposide in human milk or its effects on breastfed infant milk production. Because of the potential for serious adverse reactions in nursing infants from ETOPOPHOS, advise women not to breastfeed during treatment with ETOPOPHOS.

8.3 Females and Males of Reproductive Potential

Contraception
Females
Advise females of reproductive potential to use effective contraception during treatment with ETOPOPHOS and for 6 months after the final dose.
Males
ETOPOPHOS may damage spermatozoa and testicular tissue, resulting in possible genetic fetal abnormalities. Males with female sexual partners of reproductive potential should use effective contraception during treatment with ETOPOPHOS and for 4 months after the final dose.

Infertility
Females
In females of reproductive potential, ETOPOPHOS may cause infertility and result in amenorrhea. Premature menopause can occur with ETOPOPHOS. Recovery of menses and ovulation is related to age at treatment.
Males
In male patients, ETOPOPHOS may result in oligospermia, azoospermia, and permanent loss of fertility. Sperm counts have been reported to return to normal levels in some men, and in some cases, have occurred several years after the end of therapy [See Nonclinical Toxicology (13.1)].

8.4 Pediatric Use

Safety and effectiveness in pediatric patients have not been established.

8.5 Geriatric Use

Clinical studies of etoposide did not include sufficient numbers (n=71) of patients aged 65 years and over to determine whether they respond differently from younger patients. Other reported clinical experience has not identified differences in responses between elderly and younger patients.

10 OVERDOSAGE

No antidote has been established for ETOPOPHOS overdosage in humans. Based on animal studies, overdosage may result in neurotoxicity.

11 DESCRIPTION

ETOPOPHOS (etoposide phosphate) is a topoisomerase inhibitor. The chemical name for etoposide phosphate is: 4'-Demethylepipodophyllotoxin 9-[4,6-O-(R)-ethylidene-β-D-glucopyranoside], 4' (dihydrogen phosphate).

Etoposide phosphate has the following structure:

Etoposide phosphate is a phosphate ester of etoposide, a semi-synthetic derivative of podophyllotoxin. ETOPOPHOS is available for intravenous infusion as a sterile lyophilized powder in single-dose vials for reconstitution containing 114 mg etoposide phosphate, equivalent to 100 mg etoposide, 32.7 mg sodium citrate USP, and 300 mg dextran 40.

12 CLINICAL PHARMACOLOGY

12.1 Mechanism of Action

Etoposide phosphate is a prodrug that is converted to its active moiety, etoposide, by dephosphorylation. Etoposide causes the induction of DNA strand breaks by an interaction with DNA-topoisomerase II or the formation of free radicals, leading to cell cycle arrest, primarily at the G2 stage of the cell cycle, and cell death.

12.2 Pharmacodynamics

Following intravenous administration of 90, 100, and 110 mg/m^2 dose of ETOPOPHOS over 60 minutes, mean nadir values (expressed as percent decrease from baseline) for granulocytes, hemoglobin, and thrombocytes were 81.0 ± 16.5%, 21.4 ± 9.9%, and 44.1 ± 20.7%, respectively.

12.3 Pharmacokinetics

Following intravenous administration of an etoposide formulation, the area under the concentration time curve (AUC) and maximum plasma concentration (Cmax) values increased linearly and etoposide did not accumulate in the plasma following daily administration for 4 to 5 days.

Distribution
Following administration of an injectable etoposide formulation, the mean volume of distribution of etoposide at steady state was 18 to 29 liters.
Etoposide enters the CSF poorly.
In vitro, etoposide is 97% bound to human plasma proteins, primarily albumin.

Elimination
The terminal elimination half-life of etoposide ranges from 4 to 11 hours. Total body clearance values range from 33 to 48 mL/min.

Metabolism
Following intravenous administration of ETOPOPHOS, etoposide phosphate is completely converted to etoposide in plasma. Etoposide is metabolized by opening of the lactone ring, O-demethylation, and conjugation (i.e., glucuronidation and sulfation). O-demethylation occurs through the CYP450 3A4 isoenzyme pathway to produce the active catechol metabolite.

Excretion
At 120 hours after intravenous administration of radiolabeled etoposide formulation, the mean recovery of radioactivity in the urine was 56% of the dose, 45% of which was excreted as etoposide and 8% or less as metabolites. Fecal recovery of radioactivity was 44% of the dose.

Specific Populations
Following intravenous administration of etoposide in adults, the total body clearance of etoposide was correlated with creatinine clearance, serum albumin concentration, and non-renal clearance. No clinically significant differences in the pharmacokinetics of etoposide were observed based on age and sex.

Drug Interaction Studies
Cisplatin: Co-administration of cisplatin may increase exposure to etoposide.
Highly protein-bound drugs: Phenylbutazone, sodium salicylate, and aspirin displaced protein-bound etoposide in vitro.
Select antiepileptic medications: Co-administration with antiepileptic medications including phenytoin, phenobarbital, carbamazepine, and valproic acid may increase etoposide clearance.
Etoposide may be a substrate of the P-glycoprotein (P-gp) transporter system based upon in vitro studies.

13 NONCLINICAL TOXICOLOGY

13.1 Carcinogenesis, Mutagenesis, Impairment of Fertility

ETOPOPHOS was non-mutagenic in an in vitro Ames microbial mutagenicity assay; however, ETOPOPHOS is rapidly and completely converted to etoposide in vivo. Therefore, as etoposide is mutagenic in the Ames assay, ETOPOPHOS is considered mutagenic in vivo.

In rats, oral dosing of ETOPOPHOS for 5 consecutive days at doses greater than or equal to 86 mg/kg/day (about 10 times the 50 mg/m^2 human dose based on BSA) resulted in irreversible testicular atrophy. Irreversible testicular atrophy was also present in rats treated with ETOPOPHOS intravenously for 30 days at 5.11 mg/kg/day (about 0.5 times the 50 mg/m^2 human dose based on BSA).

14 CLINICAL STUDIES

Study 1 was a multicenter trial in patients, with previously untreated, small cell lung cancer, randomized (1:1) to receive either etoposide phosphate (80 mg/m^2/day) plus cisplatin (20 mg/m^2/day) for 5 days, or etoposide (80 mg/m^2/day) plus cisplatin (20 mg/m^2/day). The major efficacy outcome measure was objective response rate (ORR).
Among the 121 patients enrolled, the median age was 64 years, 65% of patients were male, 89% were White, and ECOG performance score was 0 to 2.
Study 1 demonstrated an overall response rate of 61% (95% confidence interval [CI] 47, 73) for patients treated with etoposide phosphate plus cisplatin, and 58% (95% CI: 45, 71) for those receiving etoposide plus cisplatin.

15 REFERENCES

1. "OSHA Hazardous Drugs." OSHA. http://www.osha.gov/SLTC/hazardousdrugs/index.html

16 HOW SUPPLIED/STORAGE AND HANDLING

How Supplied/Storage
ETOPOPHOS is supplied as a single-dose vial containing etoposide phosphate equivalent to 100 mg etoposide as a lyophilized powder for reconstitution, individually packaged in a carton:
NDC 61269-410-20
Store unopened vials at 2° to 8°C (36°-46°F). Keep vial in outer carton to protect from light.

Handling
ETOPOPHOS is a cytotoxic drug. Follow applicable special handling and disposal procedures.^1

17 PATIENT COUNSELING INFORMATION

Myelosuppression

- Advise patients that periodic monitoring of their blood counts is required. Advise patients to contact their healthcare provider for new onset of bleeding, fever, or symptoms of infection [see Warnings and Precautions (5.1)].

Embryo-Fetal Toxicity

- Advise females of reproductive potential of the potential risk to a fetus and to inform their healthcare provider of a known or suspected pregnancy [see Warnings and Precautions (5.4) and Use in Specific Populations (8.1, 8.3)].
- Advise females of reproductive potential to use effective contraception during and 6 months after treatment with ETOPOPHOS [see Warnings and Precautions (5.4) and Use in Specific Populations (8.1, 8.3)].
- Advise males with female sexual partners of reproductive potential to use condoms during treatment with ETOPOPHOS and for at least 4 months after the final dose [see Warnings and Precautions (5.4) and Use in Specific Populations (8.3)].

Licensed by:
CHEPLAPHARM Arzneimittel GmbH
17489 Greifswald, Germany

Product of Germany

Distributed by:
H2-Pharma, LLC
Montgomery, AL 36117

PACKAGE LABEL

---------------------------------------------------------------------------------------------------------
ETOPOPHOS 100 mg for Injection Representative Packaging

See How Supplied section for a complete list of available packages of ETOPOPHOS.

NDC 61269-410-20

Single-Dose Vial

ETOPOPHOS®

(etoposide phosphate) for Injection

For IV use

Etoposide phosphate equivalent to

100 mg etoposide

Rx only